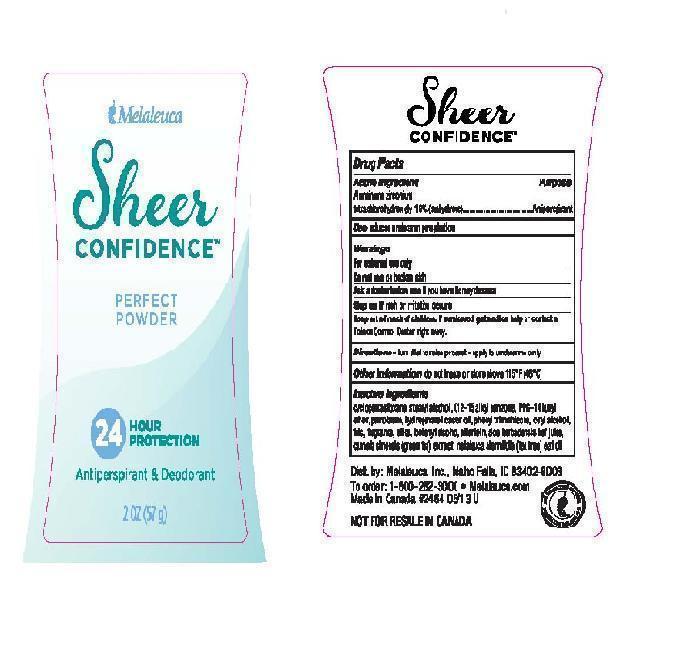 DRUG LABEL: Sheer Confidence Antiperspirant Deodorant
NDC: 54473-243 | Form: STICK
Manufacturer: Melaleuca Inc.
Category: otc | Type: HUMAN OTC DRUG LABEL
Date: 20210902

ACTIVE INGREDIENTS: ALUMINUM ZIRCONIUM TETRACHLOROHYDREX GLY 19 g/57 g
INACTIVE INGREDIENTS: ALKYL (C12-15) BENZOATE; ALLANTOIN; ALOE VERA LEAF; CETYL ALCOHOL; CYCLOMETHICONE 5; DOCOSANOL; GREEN TEA LEAF; HYDROGENATED CASTOR OIL; PETROLATUM; PHENYL TRIMETHICONE; PPG-14 BUTYL ETHER; SILICON DIOXIDE; STEARYL ALCOHOL; TALC; TEA TREE OIL

Sheer Confidence Antiperspirant Deodorant Perfect Powder

Active ingredient

Aluminum zirconium tetrachlorohydrex gly (19% Anhydrous)

Purpose

Antiperspirant

INDICATIONS AND USAGE

Use reduces underarm perspiration

Warnings

For external use only

Do not use on broken skin

ASK DOCTOR

Ask a dcotor before use if you have kidney disease

Stop use if rash or irritation occurs

Keep out of reach of children. If swallowed, get medical help or contact a Poison Control Center right away.

DOSAGE AND ADMINISTRATION

Directions ■ turn dial to raise product ■ apply to underarms only

Other information do not freeze or store above 115°F (46°C)

Inactive ingredients

cyclopentasiloxane, stearyl alcohol, C12-15 alkyl benzoate, PPG-14 butyl ether, petrolatum, hydrogenated castor oil, phenyl trimethicone, cetyl alcohol, talc, fragrance, silica, behenyl alcohol, allantoin, aloe barbadensis leaf juice, camella sinensis (green tea) leaf extract, melaleuca alternifolia (tea tree) leaf oil